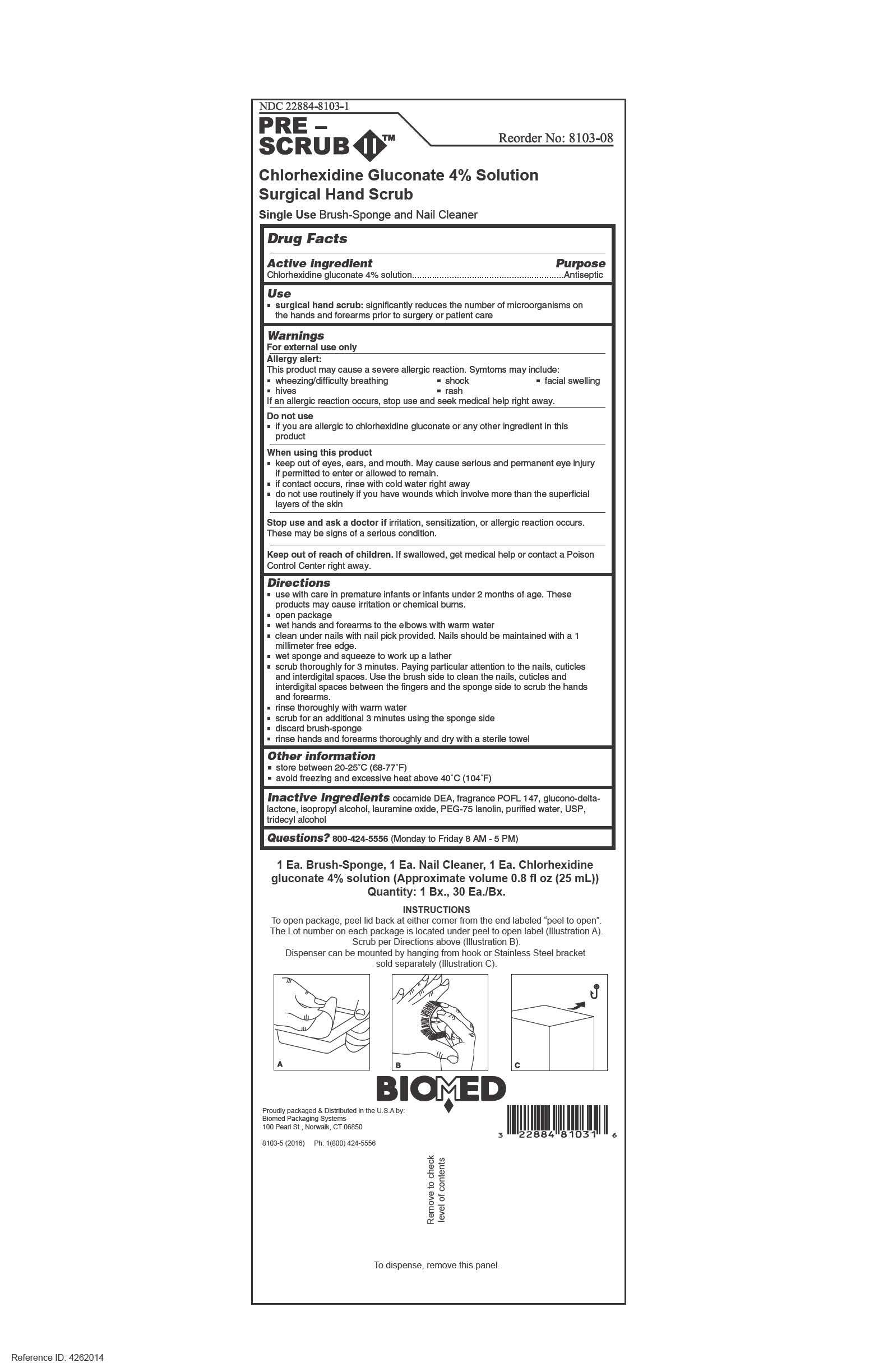 DRUG LABEL: Pre-Scrub II
NDC: 22884-8103 | Form: SOLUTION
Manufacturer: BioMed Systems, Inc.
Category: otc | Type: HUMAN OTC DRUG LABEL
Date: 20211228

ACTIVE INGREDIENTS: CHLORHEXIDINE GLUCONATE 1 mg/25 mL
INACTIVE INGREDIENTS: COCO DIETHANOLAMIDE; GLUCONOLACTONE; ISOPROPYL ALCOHOL; LAURAMINE OXIDE; POLYETHYLENE GLYCOL 3350; LANOLIN; WATER; TRIDECYL ALCOHOL

Pre-Scrub II Surgical Hand Scrub

Active Ingredient

Chlorhexidine gluconate 4% Solution

Purpose

Antiseptic

Uses

• surgical hand scrub: significantly reduces the number of micro-

organisms on the hands and forearms prior to surgery or patient care

Warnings

For external use only

____________________________________________________________________

Allergy alert:

This product may cause a severe allergic reaction. Symptoms may include:

- wheezing/difficulty breathing
- shock
- facial swelling
- hives
- rash

If an allergic reaction occurs, stop use and seek medical help right away.

____________________________________________________________________

Do not use

- If you are allergic to chlorhexidine gluconate or any other ingredient in this

product

____________________________________________________________________

When using this product

- keep out of eyes, ears, and mouth. May cause serious and permanent eye injury

if permitted to enter or allowed to remain.

- if contact occurs, rinse with cold water right away
- do not use routinely if you have wounds which involve more thank the superficial

layers of the skin

____________________________________________________________________

Stop use and ask a doctor if irritation, sensitization, or allergic reaction occurs.

These may be signs of a serious condition.

Keep out of reach of children. If swallowed, get medical help or contact a Poison Control Center right away.

Directions

• Use with care in Premature infants under 2 months of age. These

products may cause irritation or chemical burns.

• open package

• wet hands and forearms to the elbows with warm water

• clean under nails with nail pick provided. Nails should be maintained

with a 1 millimeter free edge

• wet sponge and squeeze to work up lather

• scrub thoroughly for 3 minutes. Paying particular attention to the

nails, cuticles and interdigital spaces. Use the brush side to clean the

nails, cuticles and interdigital spaces between the fingers and the

sponge side to scrub the hands and forearms

• rinse thoroughly with warm water

• scrub for an additional 3 minutes using the sponge side

• discard brush-sponge

• rinse hands and forearms thoroughly and dry with a sterile towel.

Other information

• store between 20-25ºC (68-77ºF)

•avoid freezing and excessive heat 40ºC (104ºF}

INACTIVE INGREDIENT

Inactive ingredientscocamide DEA, fragrance POFL 147, glucono-delta-lactone, isopropyl alcohol 4%, lauramine oxide, PEG-75 lanolin, purified water, USP, tridecyl alcohol

QUESTIONS

Questions? 800-424-5556 (Monday to Friday 8 AM – 5 PM)